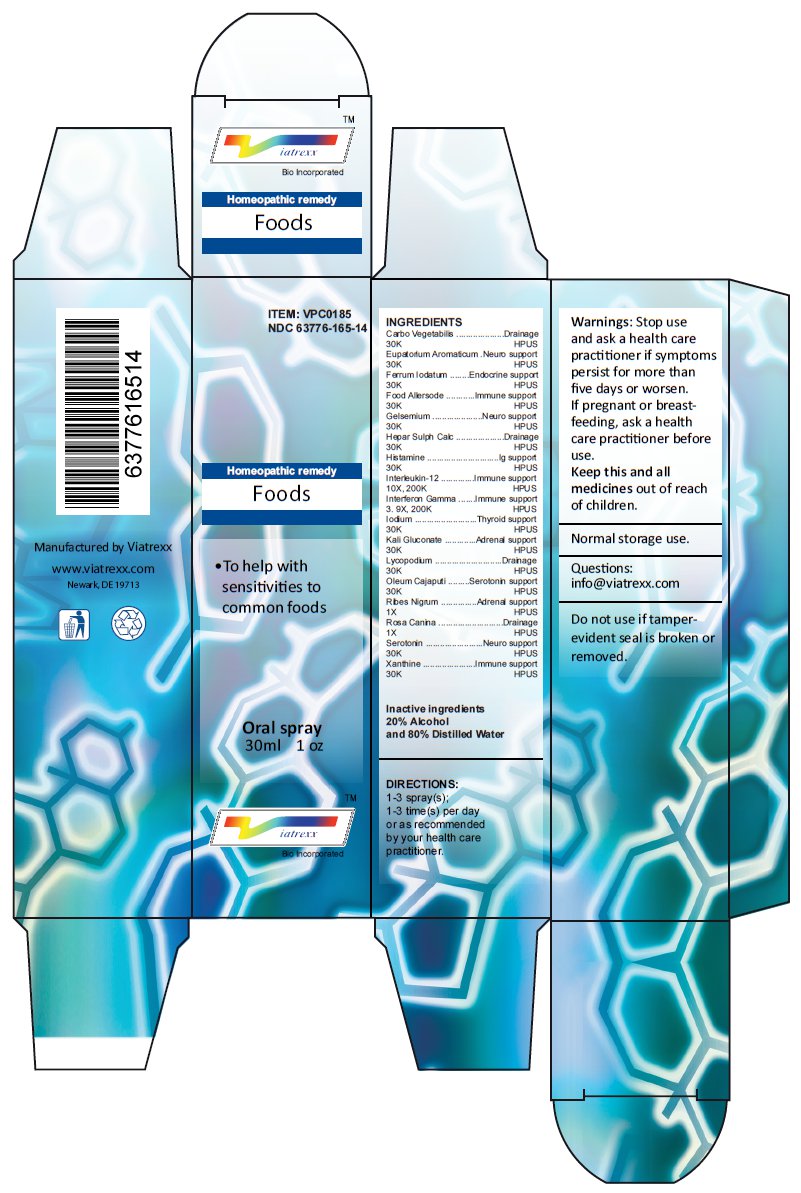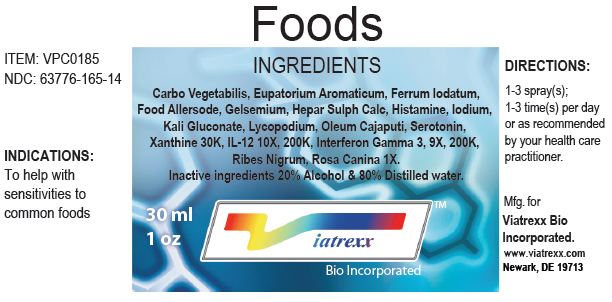 DRUG LABEL: Foods
NDC: 63776-165 | Form: SPRAY
Manufacturer: VIATREXX BIO INCORPORATED
Category: homeopathic | Type: HUMAN OTC DRUG LABEL
Date: 20230110

ACTIVE INGREDIENTS: ACTIVATED CHARCOAL 30 [kp_C]/1 mL; AGERATINA AROMATICA ROOT 30 [kp_C]/1 mL; FERROUS IODIDE 30 [kp_C]/1 mL; GELSEMIUM SEMPERVIRENS ROOT 30 [kp_C]/1 mL; CALCIUM SULFIDE 30 [kp_C]/1 mL; HISTAMINE 30 [kp_C]/1 mL; INTERLEUKIN-12 HUMAN 200 [kp_C]/1 mL; INTERFERON GAMMA-1A 200 [kp_C]/1 mL; IODINE 30 [kp_C]/1 mL; POTASSIUM GLUCONATE 30 [kp_C]/1 mL; LYCOPODIUM CLAVATUM SPORE 30 [kp_C]/1 mL; CAJUPUT OIL 30 [kp_C]/1 mL; BLACK CURRANT 1 [hp_X]/1 mL; ROSA CANINA FRUIT 1 [hp_X]/1 mL; SEROTONIN 30 [kp_C]/1 mL; XANTHINE 30 [kp_C]/1 mL; ALMOND 30 [kp_C]/1 mL; APPLE 30 [kp_C]/1 mL; BANANA 30 [kp_C]/1 mL; BARLEY 30 [kp_C]/1 mL; BEAN 30 [kp_C]/1 mL; BEEF 30 [kp_C]/1 mL; CASHEW 30 [kp_C]/1 mL; CASEIN, EMMENTAL CULTURED 30 [kp_C]/1 mL; CASEIN, LACTOCOCCUS LACTIS CULTURED 30 [kp_C]/1 mL; CASEIN, LACTOCOCCUS LACTIS CULTURED, AGED 30 [kp_C]/1 mL; CASEIN, LACTOCOCCUS LACTIS CULTURED, PENICILLIUM CAMEMBERTI CULTURED, AGED 30 [kp_C]/1 mL; CHICKEN 30 [kp_C]/1 mL; COCOA 30 [kp_C]/1 mL; COCONUT 30 [kp_C]/1 mL; COD, UNSPECIFIED 30 [kp_C]/1 mL; COFFEE BEAN 30 [kp_C]/1 mL; COTTON FIBER 30 [kp_C]/1 mL; COTTON SEED 30 [kp_C]/1 mL; ARCHED SWIMMING CRAB, COOKED 30 [kp_C]/1 mL; BLUE CRAB 30 [kp_C]/1 mL; DUNGENESS CRAB, COOKED 30 [kp_C]/1 mL; SERRATED SWIMMING CRAB, COOKED 30 [kp_C]/1 mL; SNOW CRAB, UNSPECIFIED 30 [kp_C]/1 mL; EGG 30 [kp_C]/1 mL; EGGPLANT 30 [kp_C]/1 mL; FLAX SEED 30 [kp_C]/1 mL; WHEAT GLUTEN 30 [kp_C]/1 mL; GREEN BELL PEPPER 30 [kp_C]/1 mL; HAZELNUT, UNSPECIFIED 30 [kp_C]/1 mL; LAMB 30 [kp_C]/1 mL; COW MILK 30 [kp_C]/1 mL; ONION 30 [kp_C]/1 mL; ORANGE 30 [kp_C]/1 mL; OYSTER, UNSPECIFIED 30 [kp_C]/1 mL; PEANUT 30 [kp_C]/1 mL; PECAN 30 [kp_C]/1 mL; PORK 30 [kp_C]/1 mL; POTATO 30 [kp_C]/1 mL; BROWN RICE 30 [kp_C]/1 mL; STARCH, RICE 30 [kp_C]/1 mL; WHITE RICE 30 [kp_C]/1 mL; SALMON, UNSPECIFIED 30 [kp_C]/1 mL; SHRIMP, UNSPECIFIED 30 [kp_C]/1 mL; STRAWBERRY 30 [kp_C]/1 mL; SOYBEAN 30 [kp_C]/1 mL; TEA LEAF 30 [kp_C]/1 mL; TOMATO 30 [kp_C]/1 mL; TUNA, UNSPECIFIED 30 [kp_C]/1 mL; ENGLISH WALNUT 30 [kp_C]/1 mL; WHEAT 30 [kp_C]/1 mL
INACTIVE INGREDIENTS: ALCOHOL; WATER

Foods

Active Ingredients

Carbo Vegetabilis 30K, Eupatorium Aromaticum 30K, Ferrum Iodatum 30K, Food Allersode 30K, Gelsemium 30K, Hepar Sulph Calc 30K, Histamine 30K, Interleukin-12 10X 200K, Interferon Gamma 3 9X, 200K, Iodum 30K, Kali Gluconate 30K, Lycopodium 30K, Oleum Cajaputi 30K, Ribes Nigrum 1X, Rosa Canina 1X, Serotonin 30K, Xanthine 30K

Purpose:

Carbo Vegetabilis | Drainage
Eupatorium Aromaticum | Neuro support
Ferrum Iodatum | Endocrine support
Food Allersode | Immune support
Gelsemium | Neuro support
Hepar Sulph Calc | Drainage
Histamine | Ig support
Interleukin-12 | Immune support
Interferon Gamma | Immune support
Iodium | Thyroid support
Kali Gluconate | Adrenal support
Lycopodium | Drainage
Oleum Cajaputi | Serotonin support
Ribes Nigrum | Adrenal support
Rosa Canina | Drainage
Serotonin | Neuro support
Xanthine | Immune support

Uses

To help with sensitivities to common foods

Warnings

Stop use and ask a health care practitioner if symptoms persist for more than five days or worsen. If pregnant or breastfeeding, ask a health care practitioner before use.

Dosage

1-3 spray(s); 1-3 time(s) per day or as recommended by your health care practitioner.

KEEP OUT OF REACH OF CHILDREN

Keep this and all medicines out of reach of children.

Other Ingredients

Alcohol and Water

Other Information

Normal storage use.
Do not use if tamper-evident seal is broken or removed.

Questions

info@viatrexx.com

Principal Display Panel

ITEM: VPC0185
NDC 63776-165-14
Homeopathic remedy
Foods
• To help with sensitivities to common foods
Oral spray
30ml 1 oz
Viatrexx™ Bio Incorporated
Manufactured by Viatrexx
www.viatrexx.com
Newark, DE 19713

Foods
30 mL
1 oz
Viatrexx™ Bio Incorporated
ITEM: VPC0185
NDC: 63776-165-14
INDICATIONS:
To help with sensitivities to common foods
DIRECTIONS:
1-3 spray(s); 1-3 time(s) per day or as recommended by your health care practitioner.
Mfg. for
Viatrexx Bio Incorporated.
www.viatrexx.com
Newark, DE 19713